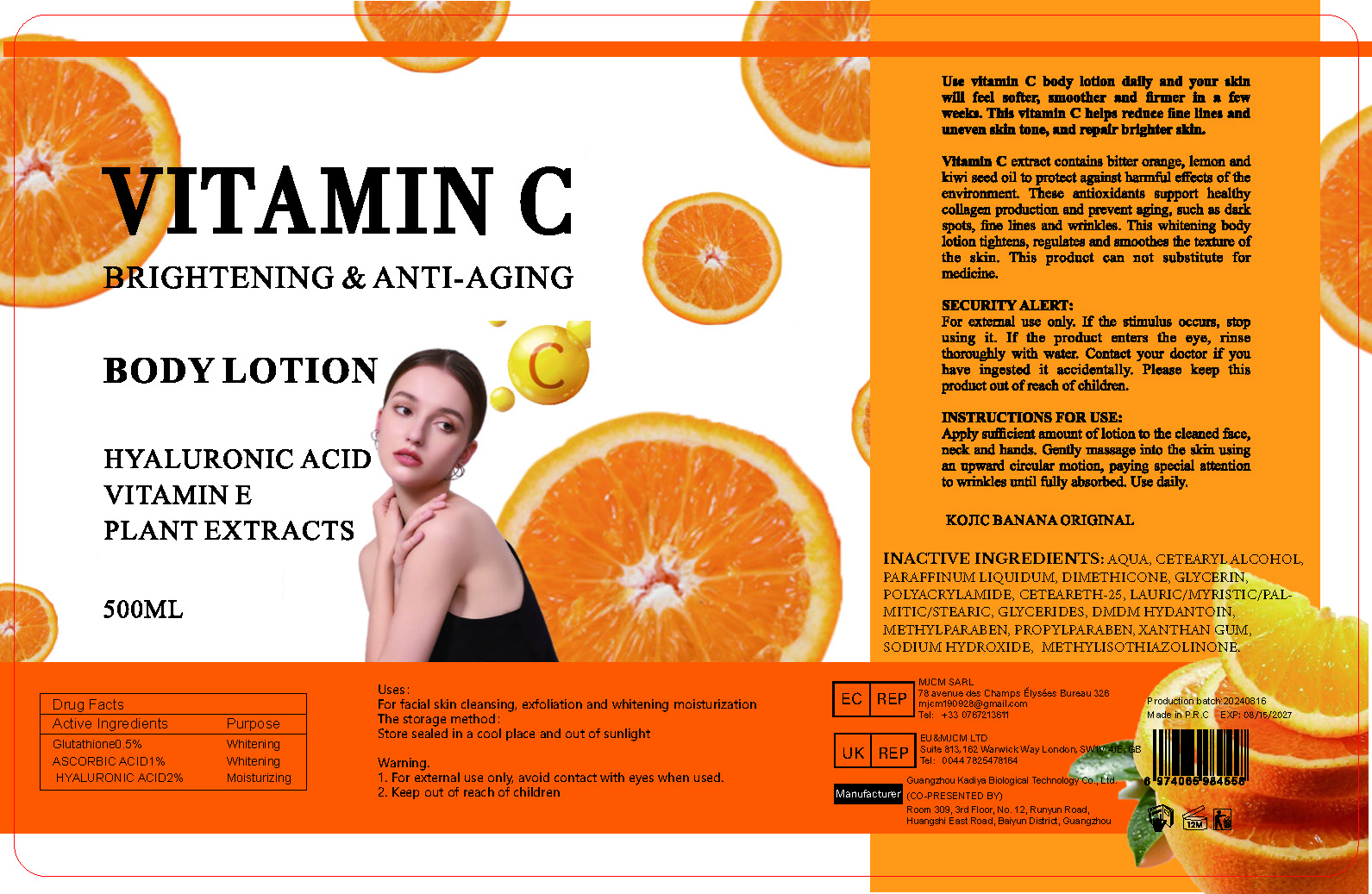 DRUG LABEL: Brightening and Anti Aging BodyLotion
NDC: 84423-042 | Form: EMULSION
Manufacturer: Guangzhou Kadiya Biotechnology Co., Ltd.
Category: otc | Type: HUMAN OTC DRUG LABEL
Date: 20240827

ACTIVE INGREDIENTS: HYALURONIC ACID 10 mg/500 mL; GLUTATHIONE 2.5 mg/500 mL; ASCORBIC ACID 5 mg/500 mL
INACTIVE INGREDIENTS: DIMETHICONE; XANTHAN GUM; WATER; METHYLPARABEN; POLYACRYLAMIDE (10000 MW); PROPYLPARABEN; CETEARETH-25; DMDM HYDANTOIN; CETOSTEARYL ALCOHOL; GLYCERIN; METHYLISOTHIAZOLINONE; SODIUM HYDROXIDE; MINERAL OIL

PURPOSE

For facial skin cleansing, exfoliation and whitening moisturization

INACTIVE INGREDIENT

AQUA、CETEARYL ALCOHOL、PARAFFINUM LIQUIDUM、DIMETHICONE、GLYCERIN、POLYACRYLAMIDE、CETEARETH-25、LAURIC/MYRISTIC/PALMITIC/STEARIC、GLYCERIDES、DMDM HYDANTOIN、METHYLPARABEN、PROPYLPARABEN、XANTHAN GUM、SODIUM HYDROXIDE、 METHYLISOTHIAZOLINONE

WARNINGS

1、For external use only, avoid contact with eyes when used
2、Keep out of reach of children

INDICATIONS AND USAGE

Use vitamin C body lotion daily and your skin will feel softer, smoother and firmer in a few weeks. This vitamin C helps reduce fine lines and uneven skin tone, and repair brighter skin.

DOSAGE AND ADMINISTRATION

Apply sufficient amount of lotion to the cleaned face, neck and hands. Gently massage into the skin using an upward circular motion, paying special attention to wrinkles until fully absorbed. Use daily

KEEP OUT OF REACH OF CHILDREN SECTION

Active Ingredients
Glutathione0.5%
ASCORBIC ACID1%
HYALURONIC ACID2%

PACKAGE LABEL

Active Ingredients
Glutathione0.5%
ASCORBIC ACID1%
HYALURONIC ACID2%

Uses：
For facial skin cleansing, exfoliation and whitening moisturization
The storage method：
Store sealed in a cool place and out of sunlight

Warning.
1、For external use only, avoid contact with eyes when used
2、Keep out of reach of children

Inactive ingredients：
AQUA、CETEARYL ALCOHOL、PARAFFINUM LIQUIDUM、DIMETHICONE、GLYCERIN、POLYACRYLAMIDE、CETEARETH-25、LAURIC/MYRISTIC/PALMITIC/STEARIC、GLYCERIDES、DMDM HYDANTOIN、METHYLPARABEN、PROPYLPARABEN、XANTHAN GUM、SODIUM HYDROXIDE、 METHYLISOTHIAZOLINONE